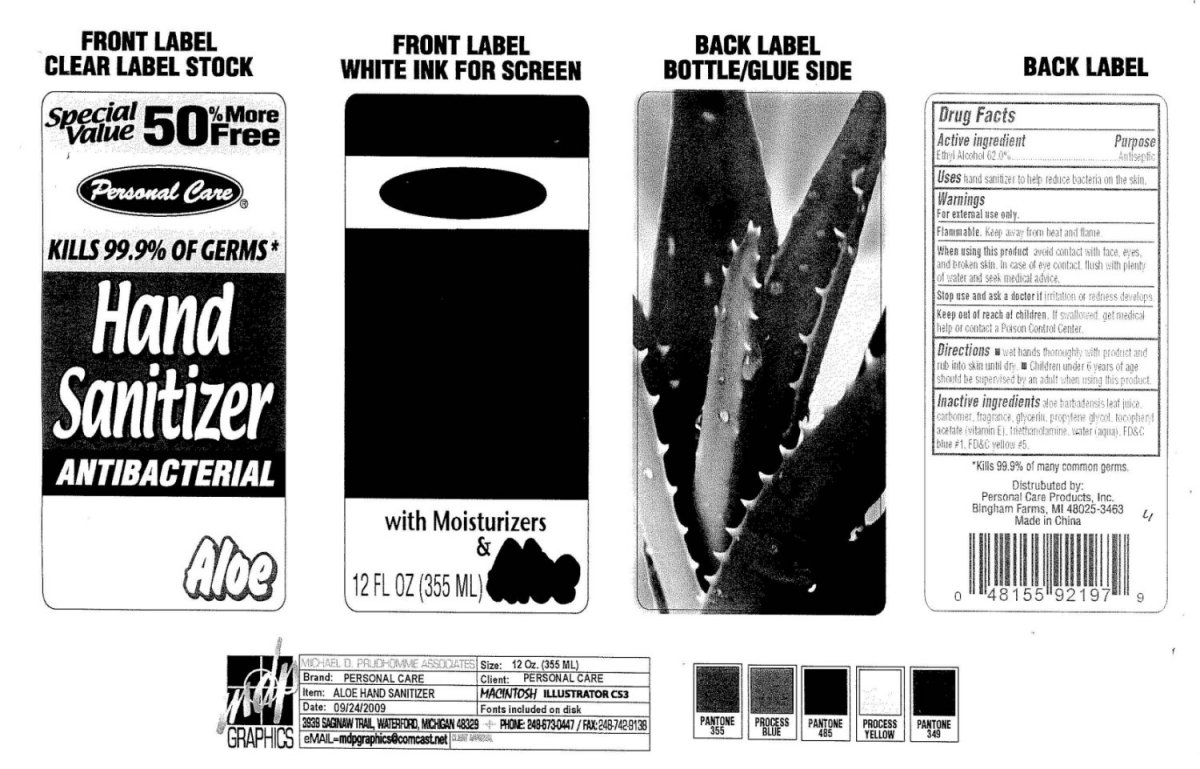 DRUG LABEL: Personal Care Hand Sanitizer Aloe
NDC: 29500-9280 | Form: GEL
Manufacturer: Personal Care Products, Inc.
Category: otc | Type: HUMAN OTC DRUG LABEL
Date: 20091009

ACTIVE INGREDIENTS: ALCOHOL 62 mL/100 mL
INACTIVE INGREDIENTS: ALOE VERA LEAF; CARBOMER HOMOPOLYMER TYPE C; GLYCERIN; PROPYLENE GLYCOL; ALPHA-TOCOPHEROL ACETATE; TROLAMINE; WATER; FD&C BLUE NO. 1; FD&C YELLOW NO. 5

Personal Care Hand Sanitizer Antibacterial Aloe

Active Ingredient Purpose

Ethyl Alcohol 62 percent Antimicrobial

Uses

hand sanitizer to help reduce bacteria on the skin.

Warnings

For external use only.

SAFE HANDLING WARNING

Flammable

Keep away from heat and flame.

When using this product avoid contact with face, eyes,

and broken skin. In case of eye contact, flush with plenty

of water and seek medical advice.

Stop use and ask a doctor if irritation or redness develops.

Keep out of reach of children. If swallowed, get medical help or contact a Poison Control Center.

Directions

wet hands thoroughly with product and rub into skin until dry.

Children under 6 years of age should be supervised by an adult when using this product.

Inactive ingredients

aloe barbadensis leaf juice,

carbomer, fragrance, glycerin, propylene glycol , tocopheryl acetate vitamin E,

triethanolamine, water aqua, FD and C blue 1, FD and C Yellow 5

DESCRIPTION

Kills 99.9 percent of many common germs.

Distributed by Personal Care Products, Inc.

Bingham Farms, MI 48025 3463

Made in China

GUARANTEED ANALYSIS OF FEED

Personal Care

Kills 99.9 percent Of Germs

Hand Sanitizer

Antibacterial

with Moisturizers

and Aloe

12 Fl oz 355 ml